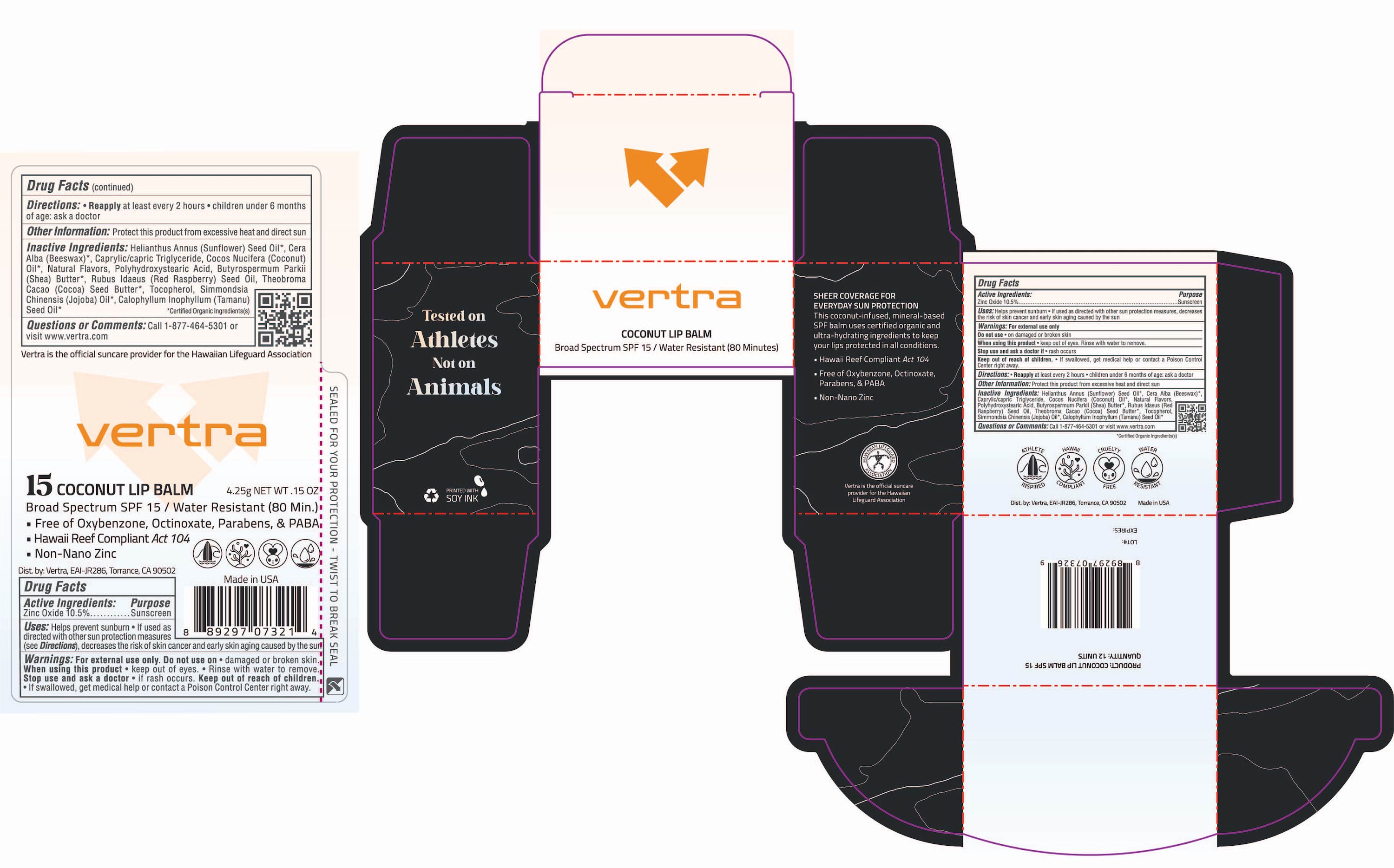 DRUG LABEL: Vertra Coconut Lip Balm Broad Spectrum SPF 15
NDC: 71014-030 | Form: STICK
Manufacturer: Eai-jr 286, Inc
Category: otc | Type: HUMAN OTC DRUG LABEL
Date: 20241022

ACTIVE INGREDIENTS: ZINC OXIDE 10.5 g/100 g
INACTIVE INGREDIENTS: SUNFLOWER OIL; WHITE WAX; JOJOBA OIL; TAMANU OIL; COCONUT OIL; POLYHYDROXYSTEARIC ACID (2300 MW); SHEA BUTTER; RASPBERRY SEED OIL; COCOA BUTTER; TOCOPHEROL; MEDIUM-CHAIN TRIGLYCERIDES

Vertra Coconut Lip Balm Broad Spectrum SPF 15

Active ingredients Purpose

Zinc Oxide 10.5% Sunscreen

Uses:

- helps Prevent Sunburn
- If used as directed with other sun protection measures (see Directions), decreases the risk of skin cancer an early skin aging caused by the sun.

Keep out of reach of children

If product is swallowed, get medical help or contact a poison Control Center right away

Stop use and ask a doctor if rash occurs

Warnings

Do not use on damaged or broken skin
When using this product keep out of eyes. Rinse with water to remove
For external use only

Directions

- Reapply at least every 2 hours.
- Children under 6 months of age: ask a doctor.

Inactive Ingredients

Helianthus Annuus (Sunflower) Seed Oil, Cera Alba (Beeswax), Caprylic/Capric Triglyceride, Cocos Nucifera (Coconut) Oil, Natural Flavors, Polyhydroxystearic Acid, Butyrospermum Pakii (Shea) Butter, Rubus Ideaus (Red Raspberry) Seed Oil, Theobroma Cocoa (Cocoa) Seed Butter, Tocopherol, Simmondsia Chinensis (Jojoba) Oil, Calophyllum Inophyllum (Tamanu) Seed Oil.

PACKAGE LABEL

vertra

Coconut Lip Balm

Broad Spectrum SPF 15 / Water Resistant (80 Minutes)

4.25g NET WT .15oz